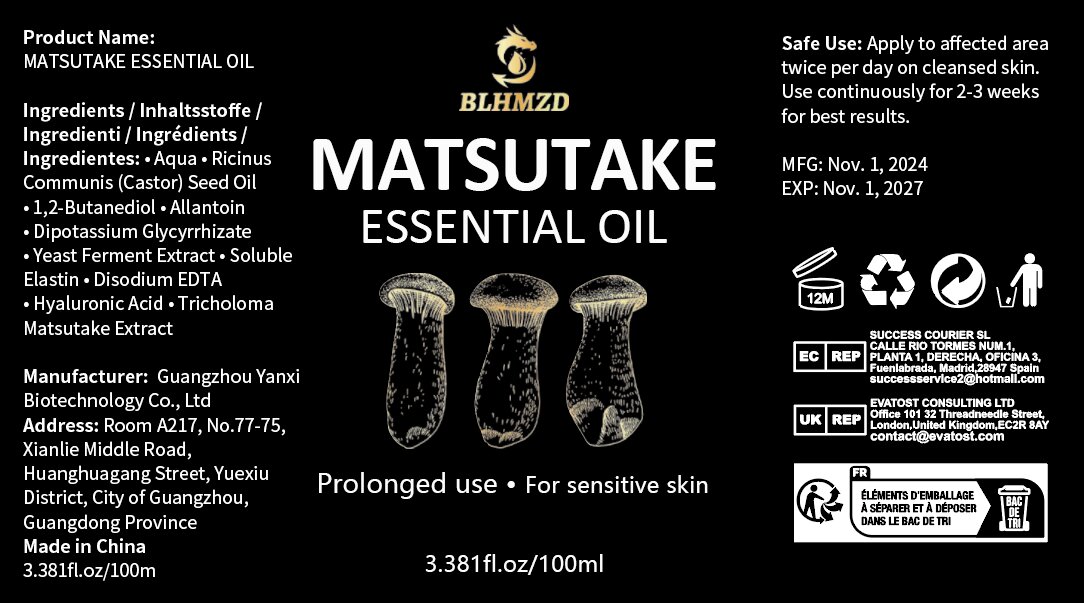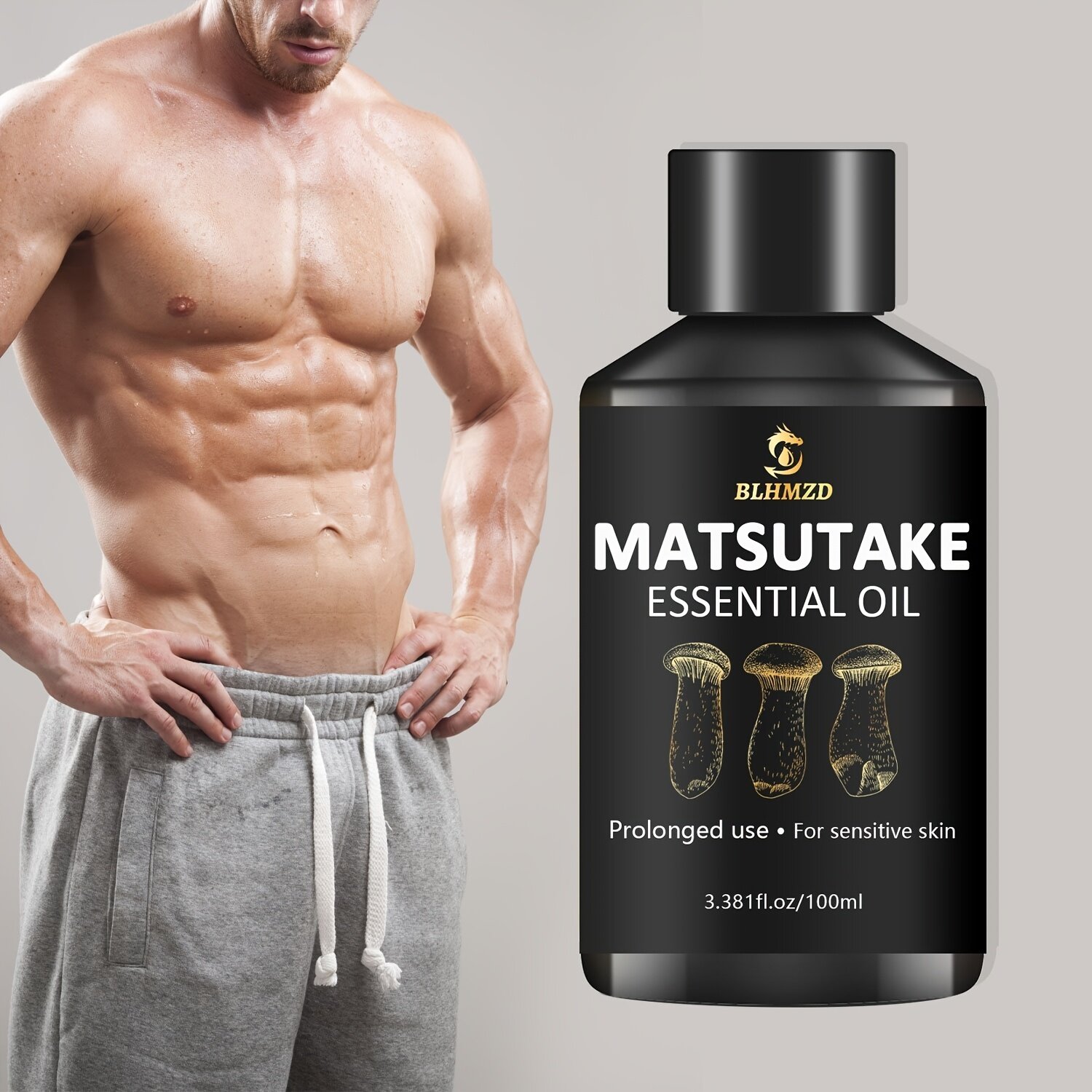 DRUG LABEL: Massage essential oil
NDC: 84025-319 | Form: OIL
Manufacturer: Guangzhou Yanxi Biotechnology Co., Ltd
Category: otc | Type: HUMAN OTC DRUG LABEL
Date: 20250109

ACTIVE INGREDIENTS: HYALURONIC ACID 3 mg/100 mL; RETINOL 5 mg/100 mL
INACTIVE INGREDIENTS: WATER

DOSAGE AND ADMINISTRATION

Apply to affected area twice per day on cleansed skin.Use continuously for 2-3 weeks for best results.

WARNINGS

keep out of children

INACTIVE INGREDIENT

Aqua

INDICATIONS AND USAGE

for daily body care

keep out of children

PURPOSE

Moisturize and nourish the body